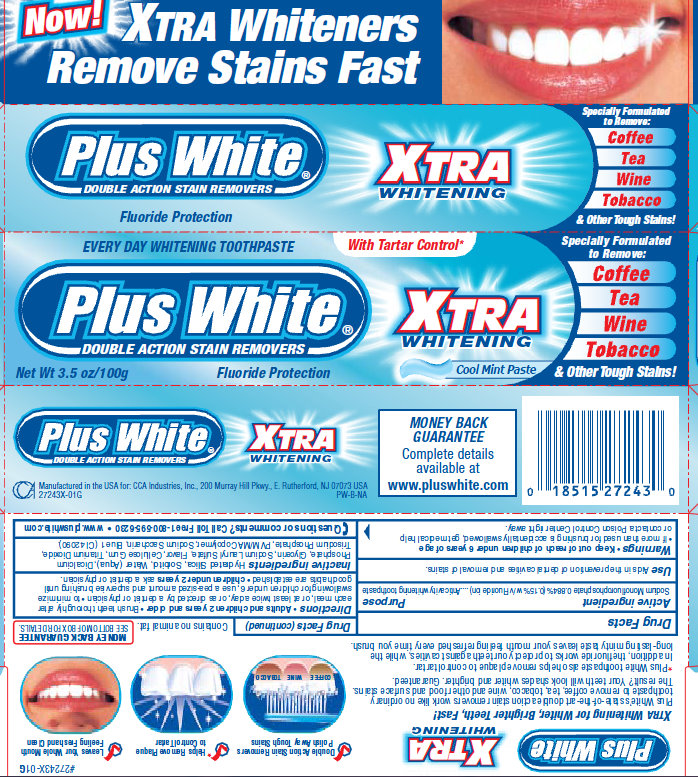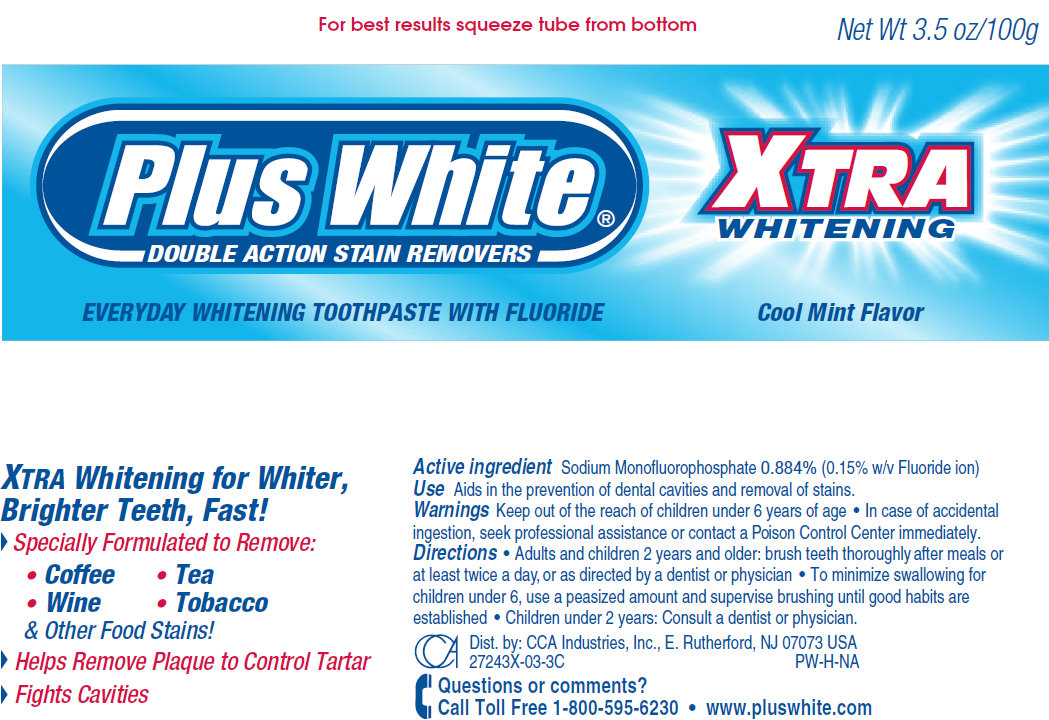 DRUG LABEL: Plus White Xtra Whitening
NDC: 61543-7243 | Form: PASTE
Manufacturer: CCA Industries, Inc.
Category: otc | Type: HUMAN OTC DRUG LABEL
Date: 20200924

ACTIVE INGREDIENTS: SODIUM MONOFLUOROPHOSPHATE 1.5 mg/1 g
INACTIVE INGREDIENTS: HYDRATED SILICA; SORBITOL; WATER; ANHYDROUS DIBASIC CALCIUM PHOSPHATE; GLYCERIN; SODIUM LAURYL SULFATE; CARBOXYMETHYLCELLULOSE SODIUM; TITANIUM DIOXIDE; SACCHARIN SODIUM; FD&C BLUE NO. 1

Plus White Xtra Whitening

Active ingredient

Sodium Monofluorophosphate 0.884% (0.15% w/v Fluoride ion)

Purpose

Anticavity whitening toothpaste

Use

Aids in the prevention of dental cavities and removal of stains

Warnings

- If more than used for brushing is accidentally swallowed, get medical help
or contact a Poison Control Center right away.

Keep out of reach of children under 6 years of age

If more than used for brushing is accidentally swallowed, get medical help or contact a Poison Control Center right away.

Directions

- Adults and children 2 years and older
- Brush teeth thoroughly after each meal, or at least twice a day, or as directed by a dentist or physician
- to minimize swallowing for children under 6, use a pea-sized amount and supervise brushing until good habits are established
- children under 2 years ask a dentist or physician.

Inactive ingredients

Hydrated Silica, Sorbitol, Water (Aqua), Dicalcium Phosphate, Glycerin, Sodium Lauryl Sulfate, Flavor, Cellulose Gum, Titanium Dioxide,

Trisodium Phosphate, PVM/MA Copolymer, Sodium Saccharin, Blue 1 (CI 42090).

Questions or comments? Call Toll Free 1-800-595-6230 - www.pluswhite.com